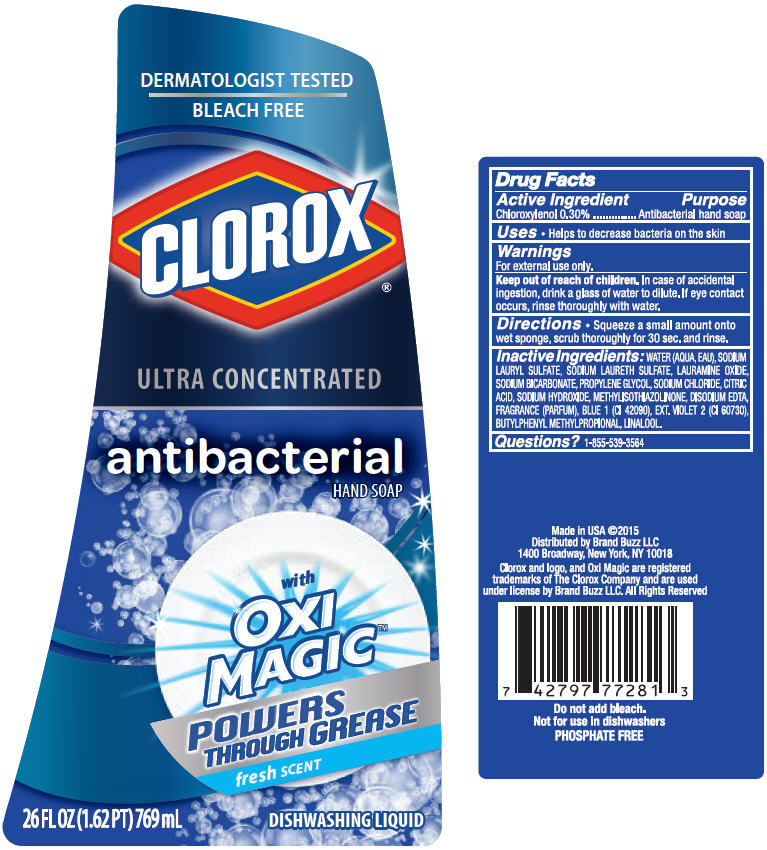 DRUG LABEL: Clorox Oxi Dish 
NDC: 69540-0018 | Form: SOAP
Manufacturer: Brand Buzz
Category: otc | Type: HUMAN OTC DRUG LABEL
Date: 20150126

ACTIVE INGREDIENTS: Chloroxylenol 0.003 g/1 mL
INACTIVE INGREDIENTS: Water; Sodium Lauryl Sulfate; Sodium Laureth-3 Sulfate; Lauramine Oxide; Sodium Bicarbonate; Propylene Glycol; Sodium Chloride; Citric Acid Monohydrate; Sodium Hydroxide; Methylisothiazolinone; Edetate Disodium; FD&C Blue No. 1; Ext. D&C Violet No. 2; Butylphenyl Methylpropional; Linalool, (+/-)-

Clorox® Oxi Dish Soap
Oxi Magic™

Drug Facts

Active Ingredient

Chloroxylenol 0.30%

Purpose

Antibacterial hand soap

Uses

- Helps to decrease bacteria on the skin

Warnings

For external use only.

Keep out of reach of children. In case of accidental ingestion, drink a glass of water to dilute. If eye contact occurs, rinse thoroughly with water.

Directions

- Squeeze a small amount onto wet sponge, scrub thoroughly for 30 sec. and rinse.

Inactive Ingredients

WATER (AQUA, EAU), SODIUM LAURYL SULFATE, SODIUM LAURETH SULFATE, LAURAMINE OXIDE, SODIUM BICARBONATE, PROPYLENE GLYCOL, SODIUM CHLORIDE, CITRIC ACID, SODIUM HYDROXIDE, METHYLISOTHIAZOLINONE, DISODIUM EDTA, FRAGRANCE (PARFUM), BLUE 1 (CI 42090), EXT. VIOLET 2 (CI 60730), BUTYLPHENYL METHYLPROPIONAL, LINALOOL.

Questions?

1-855-539-3564

Distributed by Brand Buzz LLC
1400 Broadway, New York, NY 10018

PRINCIPAL DISPLAY PANEL - 769 mL Bottle Label

DERMATOLOGIST TESTED
BLEACH FREE

CLOROX®

ULTRA CONCENTRATED

antibacterial
HAND SOAP

with
OXI
MAGIC™

POWERS
THROUGH GREASE

fresh SCENT

26 FL OZ (1.62 PT) 769 mL

DISHWASHING LIQUID